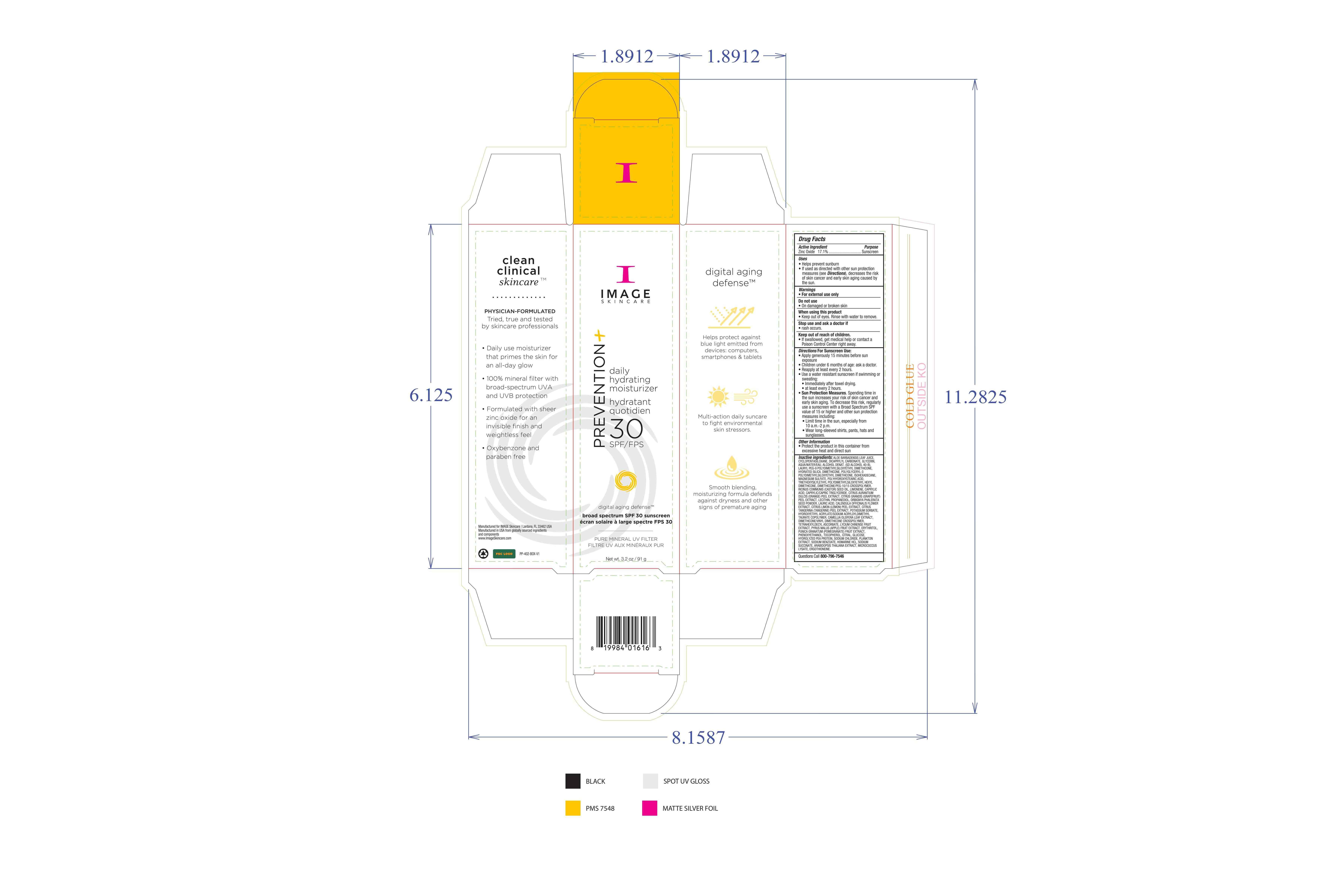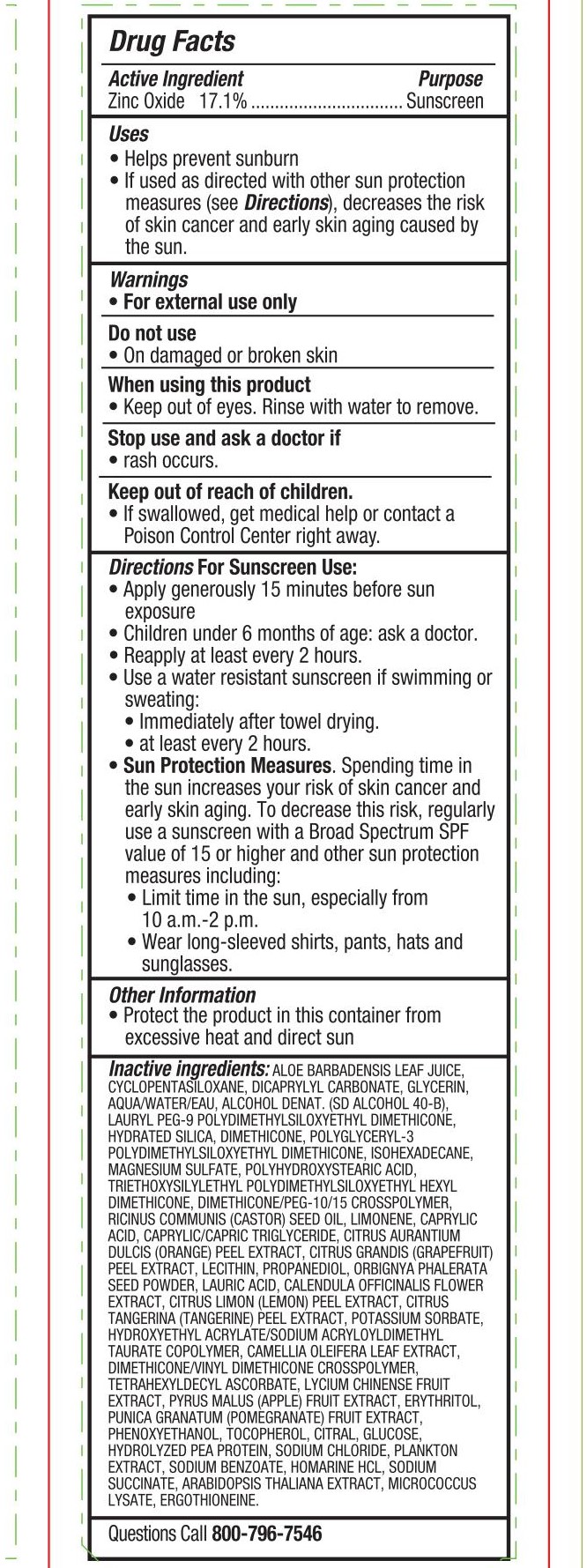 DRUG LABEL: Image Skincare Prevention Plus Daily Hydrating Moisturizer
NDC: 79458-001 | Form: CREAM
Manufacturer: Natural Technology, LLC
Category: otc | Type: HUMAN OTC DRUG LABEL
Date: 20220317

ACTIVE INGREDIENTS: ZINC OXIDE 171 g/1000 g
INACTIVE INGREDIENTS: MICROCOCCUS LUTEUS; ANACYSTIS NIDULANS EXTRACT; CYCLOMETHICONE 5; DICAPRYLYL CARBONATE; GLYCERIN; WATER; ALCOHOL; LAURYL PEG-9 POLYDIMETHYLSILOXYETHYL DIMETHICONE; PROPANEDIOL; CALENDULA OFFICINALIS FLOWER; POTASSIUM SORBATE; CAMELLIA OLEIFERA LEAF; TETRAHEXYLDECYL ASCORBATE; APPLE; ERYTHRITOL; SODIUM BENZOATE; HOMARINE HYDROCHLORIDE; SODIUM SUCCINATE HEXAHYDRATE; POLYGLYCERYL-3 POLYDIMETHYLSILOXYETHYL DIMETHICONE (4000 MPA.S); ISOHEXADECANE; MAGNESIUM SULFATE, UNSPECIFIED; POLYHYDROXYSTEARIC ACID (2300 MW); TRIETHOXYSILYLETHYL POLYDIMETHYLSILOXYETHYL HEXYL DIMETHICONE; DIMETHICONE/PEG-10/15 CROSSPOLYMER; HYDRATED SILICA; DIMETHICONE; ARABIDOPSIS THALIANA; CITRUS MAXIMA FRUIT RIND; TANGERINE PEEL; HYDROXYETHYL ACRYLATE/SODIUM ACRYLOYLDIMETHYL TAURATE COPOLYMER (100000 MPA.S AT 1.5%); DIMETHICONE/VINYL DIMETHICONE CROSSPOLYMER (SOFT PARTICLE); PEA PROTEIN; ALOE VERA LEAF; ORANGE PEEL; TOCOPHEROL; BABASSU SEED; LYCIUM CHINENSE FRUIT; PHENOXYETHANOL; CITRAL; ANHYDROUS DEXTROSE; ERGOTHIONEINE; POMEGRANATE; CASTOR OIL; LIMONENE, (+)-; CAPRYLIC ACID; MEDIUM-CHAIN TRIGLYCERIDES; LECITHIN, SOYBEAN; LAURIC ACID; LEMON PEEL; SODIUM CHLORIDE

Zinc Oxide 17.1%. Purpose: Sunscreen

91g. NDC: 79458-001-01

Purpose: Sunscreen

91 g. NDC: 79458-001-01

Helps prevent sunburn. If used as directed with other sun protection measures (see Directions), decreases the risk of skin cancer and early skin aging caused by the sun.

91g. NDC: 79458-001-01

For external use only

91 g. NDC: 79458-001-01

Do not use on damaged or broken skin.

91 g. NDC: 79458-000-06

When using this product keep out of eyes. Rinse with water to remove.

91g. NDC: 79458-001-01

Stop use and ask a doctor if rash occurs.

91g. NDC: 79458-001-01

Keep out of reach of children. If swallowed, get medical help or contact a Poison Control Center right away.

91g. NDC:79458-001-01

Apply generously 15 minutes before sun exposure. Children under 6 months of age: ask a doctor. Reapply at least every 2 hours. Use a water resistant sunscreen if swimming or sweating: Immediately after towel drying. At least every 2 hours. Sun Protection Measures. Spending time in the sun increases your risk of skin cancer and early skin aging. To decrease this risk, regularly use a sunscreen with a Broad Spectrum SPF value of 15 or higher and other sun protection measures including: limit time in the sun, especially from 10 a.m. to 2 p.m. Wear long-sleeved shirts, pants, hats and sunglasses.

91g. NDC: 79458-001-01

Protect the product in this container from excessive heat and direct sun

91g. NDC: 79458-001-01

Aloe Barbadensis Leaf Juice, Cyclopentasiloxane, Dicaprylyl Carbonate, Glycerin, Aqua/Water/Eau, Alcohol Denat. (SD Alcohol 40-B), Lauryl PEG-9 Polydimethylsiloxyethyl Dimethicone, Hydrated Silica, Dimethicone, Polyglyceryl-3 Polydimethylsiloxyethyl Dimethicone, Isohexadecane, Magnesium Sulfate, Polyhydroxystearic Acid, Triethoxysilylethyl Polydimethylsiloxyethyl Hexyl Dimethicone, Dimethicone/PEG-10/15 Crosspolymer, Ricinus Communis (Castor) Seed Oil, Limonene, Caprylic Acid, Caprylic/Capric Triglyceride, Citrus Aurantium Dulcis (Orange) Peel Extract, Citrus Grandis (Grapefruit) Peel Extract, Lecithin, Propanediol, Orbignya Phalerata Seed Powder, Lauric Acid, Calendula Officinalis Flower Extract, Citrus Limon (Lemon) Peel Extract, Citrus Tangerina (Tangerine) Peel Extract, Potassium Sorbate, Hydroxyethyl Acrylate/Sodium Acryloydimethyl Taurate Copolymer, Camellia Oleifera Leaf Extract, Dimethicone/Vinyl Dimethicone Crosspolymer, Tetrahexyldecyl Ascorbate, Lycium Chinense Fruit Extract, Pyrus Malus (Apple) Fruit Extract, Erythritol, Punica Granatum (Pomegranate) Fruit Extract, Phenoxyethanol, Tocopherol, Citral, Glucose, Hydrolyzed Pea Protein, Sodium Chloride, Plankton Extract, Sodium Benzoate, Homarine HCL, Sodium Succinate, Arabidopsis Thaliana Extract, Micrococcus Lysate, Ergothioneine.

91g. NDC: 79458-001-01

Prevention plus daily hydrating moisturizer 30 SPF/FPS

91g. NDC: 79458-001-01